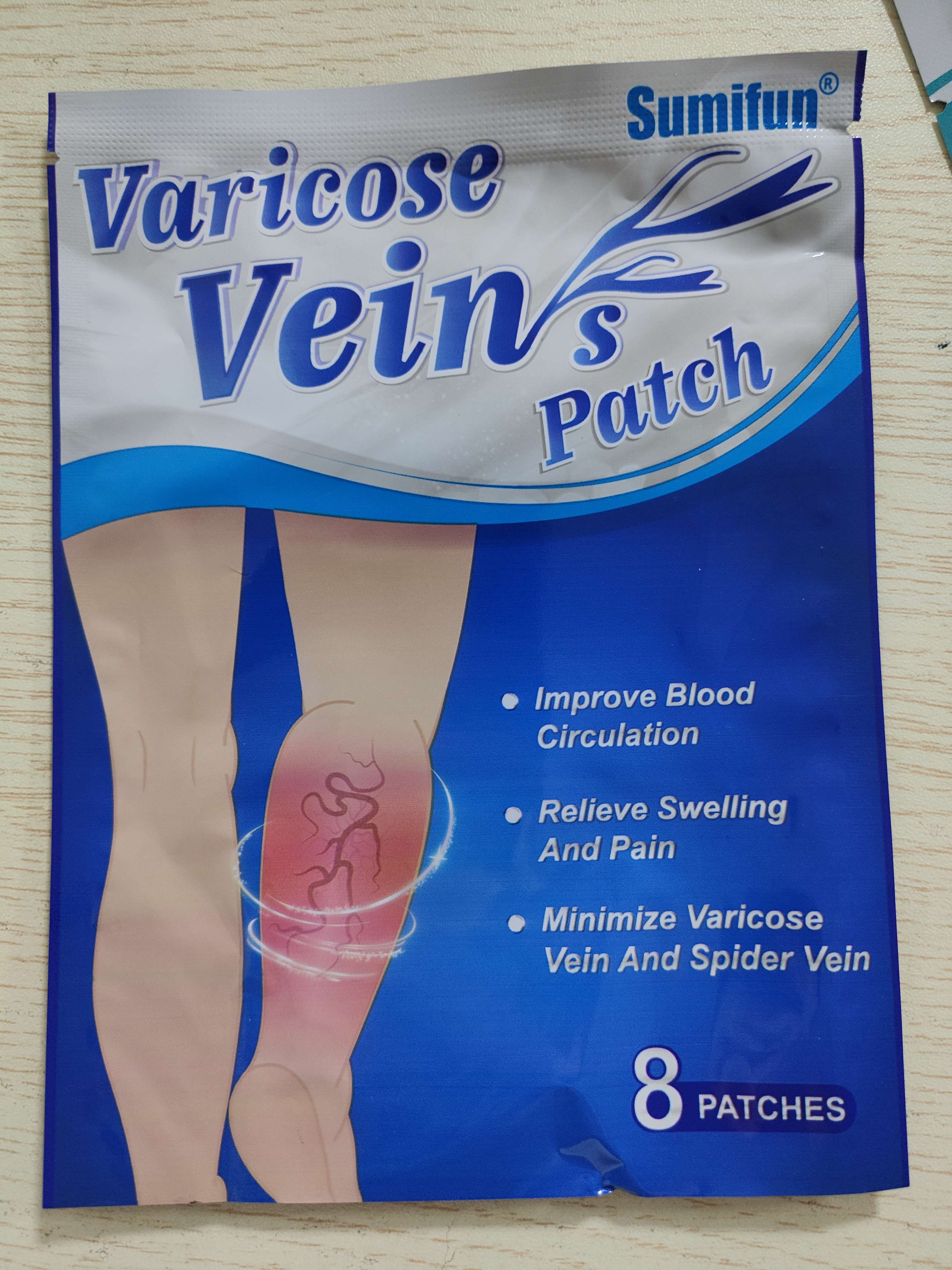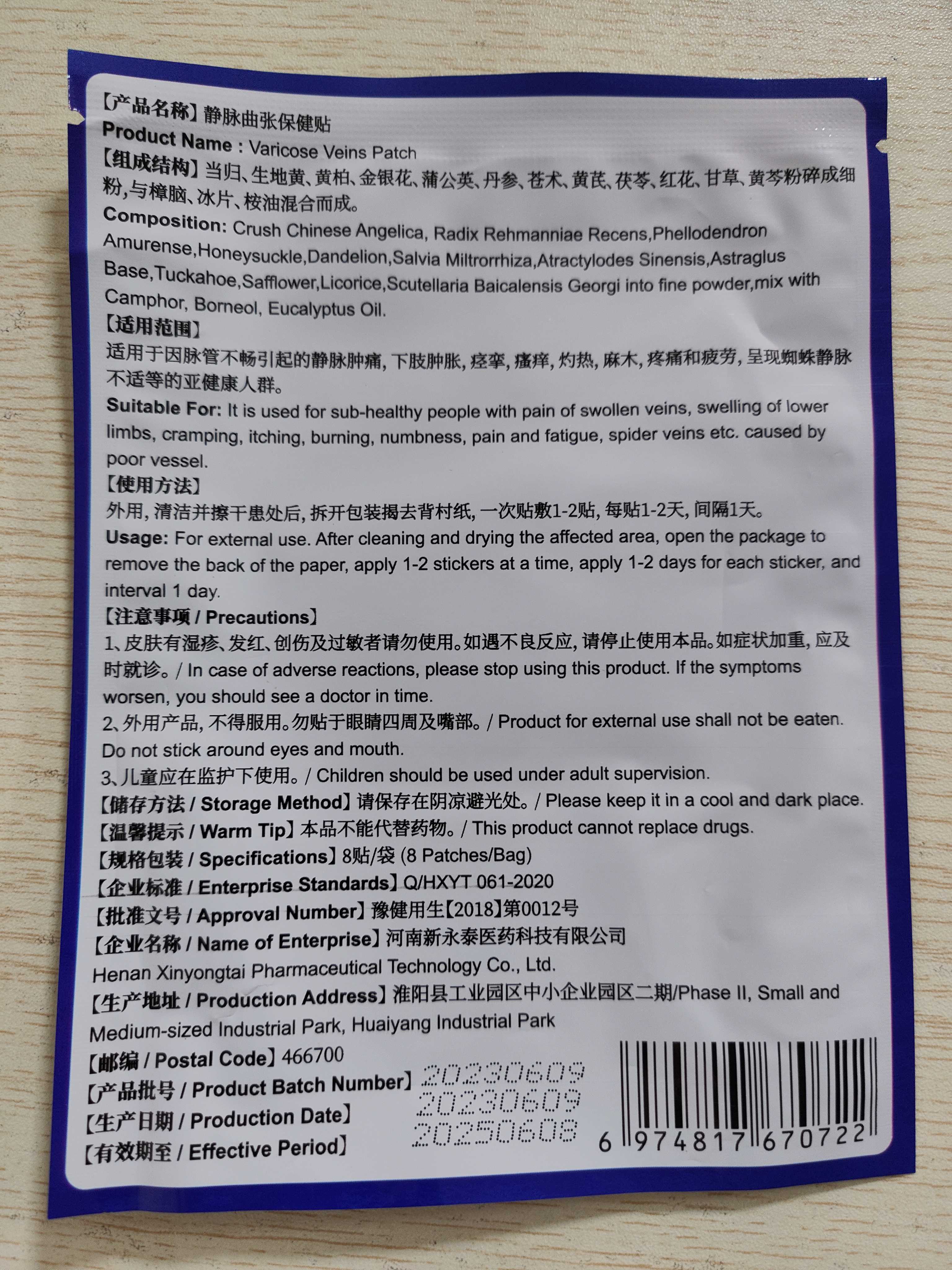 DRUG LABEL: Varicose Veins Patch
NDC: 83675-002 | Form: PATCH
Manufacturer: Guangzhou Hanhai Trading Co., Ltd
Category: otc | Type: HUMAN OTC DRUG LABEL
Date: 20230913

ACTIVE INGREDIENTS: BORNEOL 12 g/100 1
INACTIVE INGREDIENTS: TARAXACUM OFFICINALE; SAFFLOWER; LONICERA CONFUSA FLOWER; REHMANNIA GLUTINOSA ROOT; CAMPHOR (NATURAL); LICORICE; EUCALYPTUS OIL; PHELLODENDRON AMURENSE BARK; SALVIA MILTIORRHIZA WHOLE; ATRACTYLODES LANCEA ROOT; ASTRAGALUS ALLOCHROUS WHOLE; ANGELICA SINENSIS ROOT; FU LING; SCUTELLARIA BAICALENSIS WHOLE

Active Ingredient

Bormeol 12.0%

Purpose

Relieve Pain

Use

Varicose Veins Patch to help relieve pain on leg

Warnings

For external use only.

Keep Out Of Reach Of Children
Pregnant, breast-feeding, people with severe chronic diseases or allergic to the raw materials are forbidden to use

Do not use

Product shall not be eat

When Using

Do not stick around eyes and mouth,This product cannot replace drugs.

Ask Doctor

ask doctor in case of adverse reactions

Keep Oot Of Reach Of Children

Please do not place this product in a place where unconscious people can access it.

Directions

After cleaning and drying the affected area, open the package to remove the back of the paper, apply 1-2 stickers at a time, apply 1-2 days for each sticker, and interval 1 day.

Children should be used under adult supervision.

Other information

Store the product in a cool, dry and well-ventilated place

Avoid direct sunlight

Inactive ingredients

Crush Chinese Angelica

Radix Rehmanniae Recens
Phellodendron Amurense
Honeysuckle
Dandelion
Salvia Militrorrhiza
Atractylodes Sinensis
AstraglusBase
Tuckahoe
Safflower
Licorice
Scutellaria Baicalensis Georgi into fine powder
mix with Camphor
Eucalyptus Oil